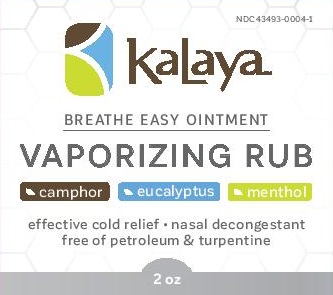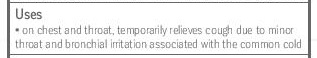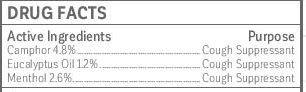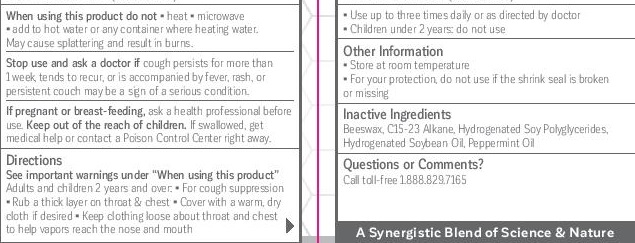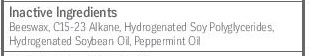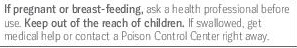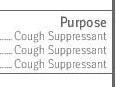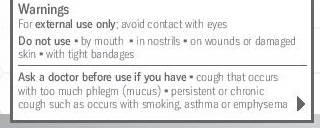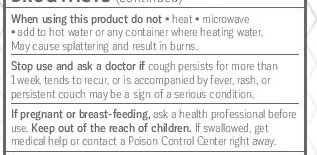 DRUG LABEL: Kalaya Breathe Easy Vaporizing Rub
NDC: 43493-0004 | Form: OINTMENT
Manufacturer: Avaria Health & Beauty Corp
Category: otc | Type: HUMAN OTC DRUG LABEL
Date: 20251008

ACTIVE INGREDIENTS: MENTHOL 26 g/100 g; CAMPHOR (NATURAL) 48 g/100 g; EUCALYPTUS OIL 12 g/100 g
INACTIVE INGREDIENTS: C15-23 ALKANE; HYDROGENATED SOYBEAN OIL; PEPPERMINT OIL; WHITE WAX

Kalaya Breathe Easy Ointment
Vaporizing Rub